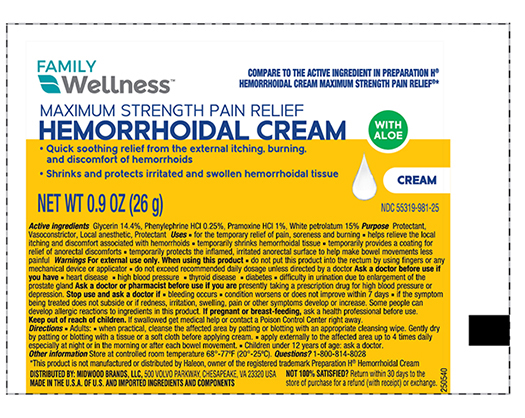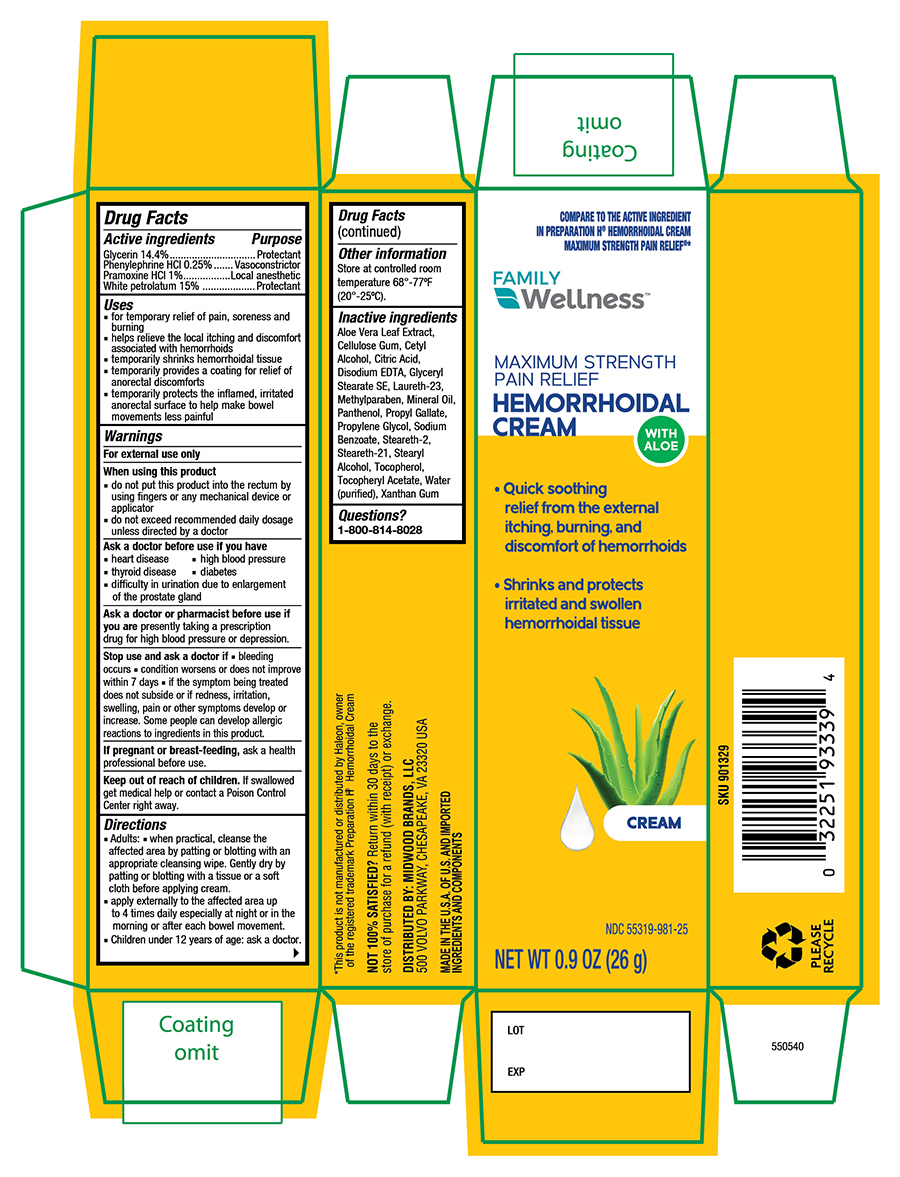 DRUG LABEL: Family Wellness HEMORRHOID
NDC: 55319-981 | Form: CREAM
Manufacturer: FAMILY DOLLAR (Family Wellness)
Category: otc | Type: HUMAN OTC DRUG LABEL
Date: 20231211

ACTIVE INGREDIENTS: GLYCERIN 144 mg/1 g; PHENYLEPHRINE HYDROCHLORIDE 2.5 mg/1 g; PRAMOXINE HYDROCHLORIDE 10 mg/1 g; PETROLATUM 150 mg/1 g
INACTIVE INGREDIENTS: GLYCERYL STEARATE SE; CETYL ALCOHOL; STEARYL ALCOHOL; STEARETH-2; STEARETH-21; CARBOXYMETHYLCELLULOSE; EDETATE DISODIUM; XANTHAN GUM; SODIUM BENZOATE; TOCOPHEROL; METHYLPARABEN; LIGHT MINERAL OIL; PROPYL GALLATE; PROPYLENE GLYCOL; LAURETH-23; ANHYDROUS CITRIC ACID; .ALPHA.-TOCOPHEROL ACETATE; ALOE VERA LEAF; PANTHENOL; WATER

Family Wellness HEMORRHOID MAX STRENGTH CREAM

Active ingredient

Glycerin 14.4%

Phenylephrine HCl 0.25%

Pramoxine HCl 1%

White petrolatum 15%

Pupose

Protectant

Vasoconstrictor

Local anesthetic

Protectant

Uses

- for temporary relief of pain, soreness and burning
- helps relieve the local itching and discomfort associated with hemorrhoids
- temporarily shrinks hemorrhoidal tissue
- temporarily provides a coating for relief of anorectal discomforts
- temporarily protects the inflamed, irritated anorectal surface to help make bowel movements less painful

Warnings

For external use only

Ask a doctor before use if you have

- heart disease
- high blood pressure
- thyroid disease
- diabetes
- difficulty in urination due to enlargement of the prostate gland

Ask a doctor or pharmacist before useif you are presently taking a prescription drug for high blood pressure or depression.

When using this product

- do not exceed the recommended daily dosage unless directed by a doctor
- do not put into the rectum by using fingers or any mechanical device or applicator

Stop use and ask a doctor if

- bleeding occurs
- condition worsens or does not improve within 7 days
- an allergic reaction develops
- the symptom being treated does not subside or if redness, irritation, swelling, pain, or other symptoms develop or increase

If pregnant or breast-feeding,ask a health professional before use.

Keep out of reach of children.If swallowed, get medical help or contact a Poison Control Center right away.

Directions

- Adults: when practical, cleanse the affected area by patting or blotting with an appropriate cleansing wipe. Gently dry by patting or blotting with a tissue or a soft cloth before applying cream.
- when first opening the tube, puncture foil seal with top end of cap
- apply externally or in the lower portion of the anal canal only
- apply externally to the affected area up to 4 times daily, especially at night, in the morning or after each bowel movement
- for application in the lower anal canal: remove cover from dispensing cap. Attach dispensing cap to tube. Lubricate dispensing cap well, then gently insert dispensing cap partway into the anus.
- thoroughly cleanse dispensing cap after each use and replace cover
- children under 12 years of age: ask a doctor

Other Information

store at controlled room temperature 68-77°F (20-25°C)

Inactive Ingredients:

Aloe Vera Leaf, Cellulose Gum, Cetyl Alcohol, Citric Acid, Disodium EDTA, Glyceryl Stearate SE, Laureth-23, Methylparaben, Mineral Oil, Panthenol, Propyl Gallate, Propylene Glycol, Sodium Benzoate, Steareth-2, Steareth-21, Stearyl Alcohol, Tocopherol, Tocopheryl Acetate, Water (purified), Xanthan Gum

Principal Display Panel

FamilyWellness NDC 55319-981-25Maxium Strength Hemmorodial Cream NET WT 0.9oz (26g)